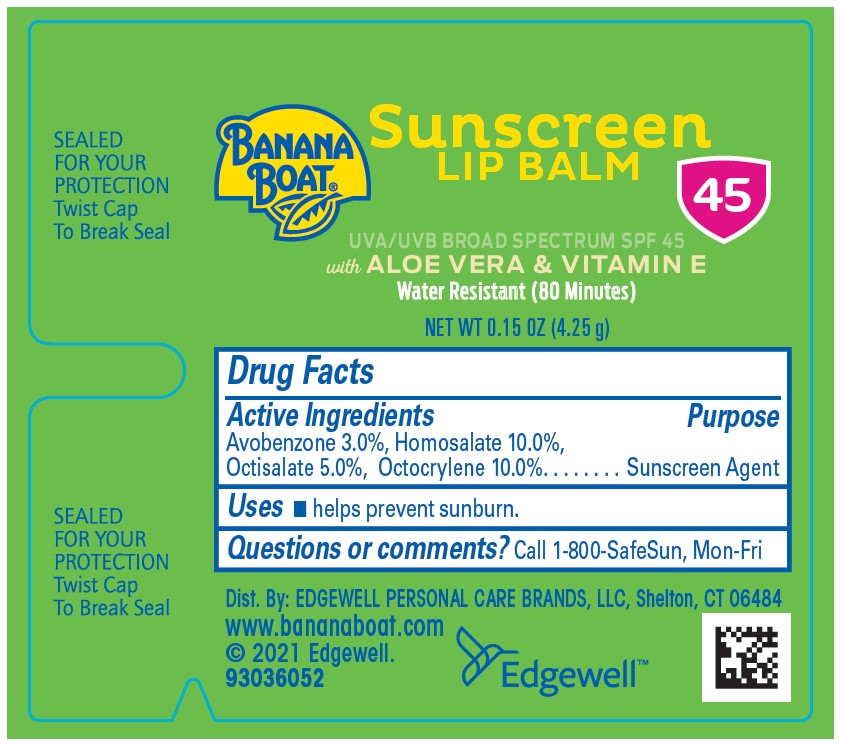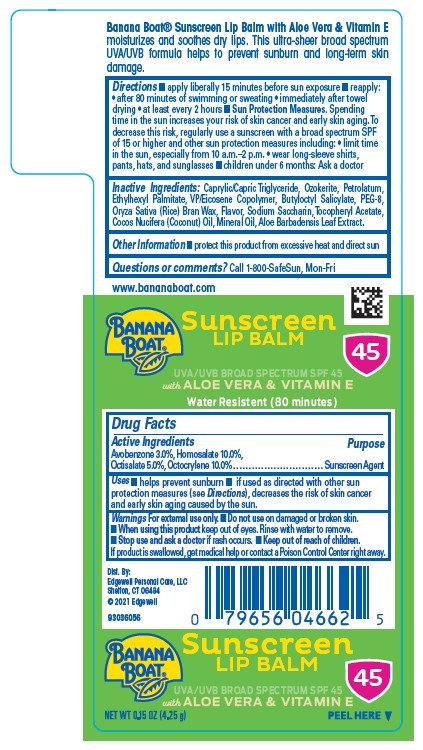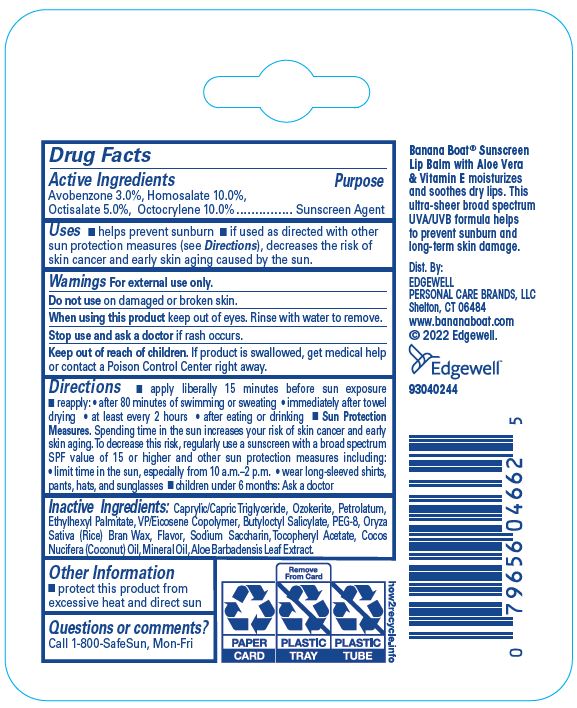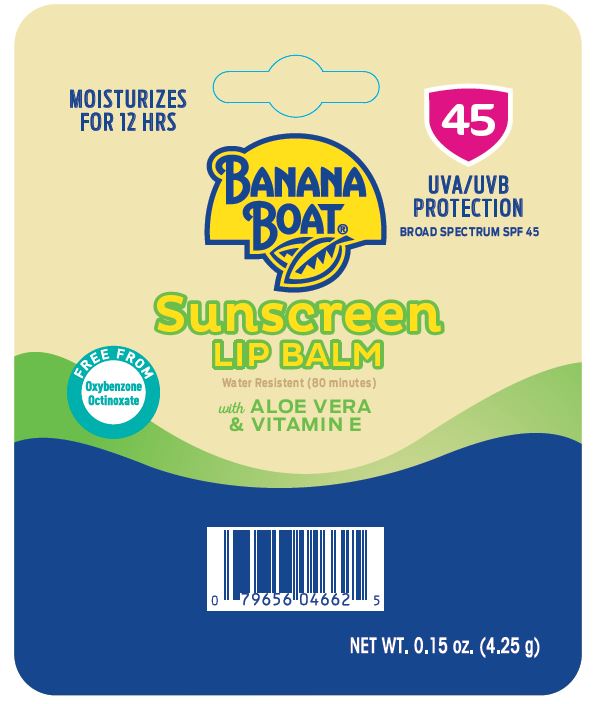 DRUG LABEL: Banana Boat Sunscreen Lip Balm UVA/UVB Broad Spectrum SPF 45
NDC: 63354-971 | Form: STICK
Manufacturer: Edgewell Personal Care Brands LLC
Category: otc | Type: HUMAN OTC DRUG LABEL
Date: 20251106

ACTIVE INGREDIENTS: OCTOCRYLENE 10 g/100 g; HOMOSALATE 10 g/100 g; AVOBENZONE 3 g/100 g; OCTISALATE 5 g/100 g
INACTIVE INGREDIENTS: SACCHARIN SODIUM ANHYDROUS; .ALPHA.-TOCOPHEROL ACETATE; COCONUT OIL; ALOE VERA LEAF; MEDIUM-CHAIN TRIGLYCERIDES; ETHYLHEXYL PALMITATE; POLYETHYLENE GLYCOL 400; RICE BRAN; MINERAL OIL; CERESIN; VINYLPYRROLIDONE/EICOSENE COPOLYMER; BUTYLOCTYL SALICYLATE; PETROLATUM

Active Ingredients

Avobenzone 3.0%, Homosalate 10.0%, Octisalate 5.0%, Octocrylene 10.0%

Purpose

Sunscreen Agent

Uses

• helps prevent sunburn • if used as directed with other sun protection measures (see Directions), decreases the risk of skin cancer and early skin aging caused by the sun.

Warnings

For external use only.

Do not use

on damaged or broken skin.

When using this product

keep out of eyes. Rinse with water to remove.

Stop use and ask a doctor

if rash occurs.

Keep out of reach of children.

If product is swallowed, get medical help or contact a Poison Control Center right away.

Directions

• apply liberally 15 minutes before sun exposure • reapply: • after 80 minutes of swimming or sweating • immediately after towel drying • at least every 2 hours • after eating or drinking • Sun Protection Measures. Spending time in the sun increases your risk of skin cancer and early skin aging. To decrease this risk, regularly use a sunscreen with a broad spectrum SPF value of 15 or higher and other sun protection measures including: • limit time in the sun, especially from 10 a.m.–2 p.m. • wear long-sleeved shirts, pants, hats, and sunglasses • children under 6 months: Ask a doctor

Inactive Ingredients

Caprylic/Capric Triglyceride, Ozokerite, Petrolatum, Ethylhexyl Palmitate, VP/Eicosene Copolymer, Butyloctyl Salicylate, PEG-8, Oryza Sativa (Rice) Bran Wax, Flavor, Sodium Saccharin, Tocopheryl Acetate, Cocos Nucifera (Coconut) Oil, Mineral Oil, Aloe Barbadensis Leaf Extract.

Other Information

protect this product from excessive heat and direct sun

Questions or comments?

Call 1-800-SafeSun, Mon-Fri

Principal Display Panel

MOISTURIZES
FOR 12 HRS
BANANA
BOAT®
45
UVA/UVB
PROTECTION
BROAD SPECTRUM SPF 45
Sunscreen
LIP BALM
Water Resistent (80 minutes)
with ALOE VERA
& VITAMIN E
FREE FROM
Oxybenzone
Octinoxate
NET WT. 0.15 oz. (4.25 g)

BANANA
BOAT®
Sunscreen
LIP BALM
45
UVA/UVB BROAD SPECTRUM SPF 45
with ALOE VERA & VITAMIN E
Water Resistent (80 minutes)

BANANA
BOAT®
Sunscreen
LIP BALM
45
UVA/UVB BROAD SPECTRUM SPF 45
with ALOE VERA & VITAMIN E
NET WT 0.15 OZ (4.25 g) PEEL HERE